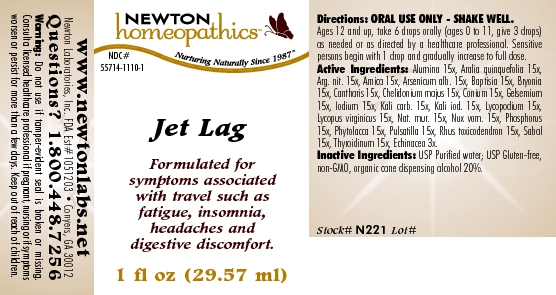 DRUG LABEL: Jet Lag 
NDC: 55714-1110 | Form: LIQUID
Manufacturer: Newton Laboratories, Inc.
Category: homeopathic | Type: HUMAN OTC DRUG LABEL
Date: 20110301

ACTIVE INGREDIENTS: Aluminum Oxide 15 [hp_X]/1 mL; American Ginseng 15 [hp_X]/1 mL; Silver Nitrate 15 [hp_X]/1 mL; Arnica Montana 15 [hp_X]/1 mL; Arsenic Trioxide 15 [hp_X]/1 mL; Baptisia Tinctoria 15 [hp_X]/1 mL; Bryonia Alba Root 15 [hp_X]/1 mL; Lytta Vesicatoria 15 [hp_X]/1 mL; Chelidonium Majus 15 [hp_X]/1 mL; Conium Maculatum Flowering Top 15 [hp_M]/1 mL; Gelsemium Sempervirens Root 15 [hp_X]/1 mL; Iodine 15 [hp_X]/1 mL; Potassium Carbonate 15 [hp_X]/1 mL; Potassium Iodide 15 [hp_X]/1 mL; Lycopodium Clavatum Spore 15 [hp_X]/1 mL; Lycopus Virginicus 15 [hp_X]/1 mL; Sodium Chloride 15 [hp_X]/1 mL; Strychnos Nux-vomica Seed 15 [hp_X]/1 mL; Phosphorus 15 [hp_X]/1 mL; Phytolacca Americana Root 15 [hp_X]/1 mL; Pulsatilla Vulgaris 15 [hp_X]/1 mL; Toxicodendron Pubescens Leaf 15 [hp_X]/1 mL; Saw Palmetto 15 [hp_X]/1 mL; Thyroid, Unspecified 15 [hp_X]/1 mL; Echinacea, Unspecified 3 [hp_X]/1 mL
INACTIVE INGREDIENTS: Alcohol

Jet Lag

INDICATIONS & USAGE SECTION

Jet Lag Formulated for symptoms associated with travel such as fatigue, insomnia, headaches and digestive discomfort.

DOSAGE & ADMINISTRATION SECTION

Directions: ORAL USE ONLY - SHAKE WELL. Ages 12 and up, take 6 drops orally (ages 0 to 11, give 3 drops) as needed or as directed by a healthcare professional. Sensitive persons begin with 1 drop and gradually increase to full dose.

OTC - ACTIVE INGREDIENT SECTION

Alumina 15x, Aralia quinquefolia 15x, Arg. nit. 15x, Arnica 15x, Arsenicum alb. 15x, Baptisia 15x, Bryonia 15x, Cantharis 15x, Chelidonium majus 15x, Conium 15x, Gelsemium 15x, Iodium 15x, Kali carb. 15x, Kali iod. 15x, Lycopodium 15x, Lycopus virginicus 15x, Nat. mur. 15x, Nux vom. 15x, Phosphorus 15x, Phytolacca 15x, Pulsatilla 15x, Rhus toxicodendron 15x, Sabal 15x, Thyroidinum 15x, Echinacea 3x.

OTC - PURPOSE SECTION

Formulated for symptoms associated with travel such as fatigue, insomnia, headaches and digestive discomfort.

INACTIVE INGREDIENT SECTION

Inactive Ingredients: USP Purified Water; USP Gluten-free, non-GMO, organic cane dispensing alcohol 20%.

QUESTIONS SECTION

www.newtonlabs.net Newton Laboratories, Inc. FDA Est # 1051203 - Conyers, GA 30012
Questions? 1.800.448.7256

WARNINGS SECTION

Warning: Do not use if tamper - evident seal is broken or missing. Consult a licensed healthcare professional if pregnant, nursing or if symptoms worsen or persist for more than a few days. Keep out of reach of children.

OTC - PREGNANCY OR BREAST FEEDING SECTION

Consult a licensed healthcare professional if pregnant, nursing or if symptoms worsen or persist for more than a few days.

OTC - KEEP OUT OF REACH OF CHILDREN SECTION

Keep out of reach of children.